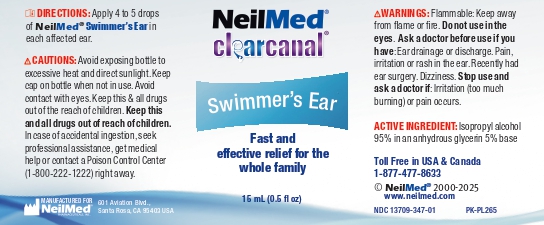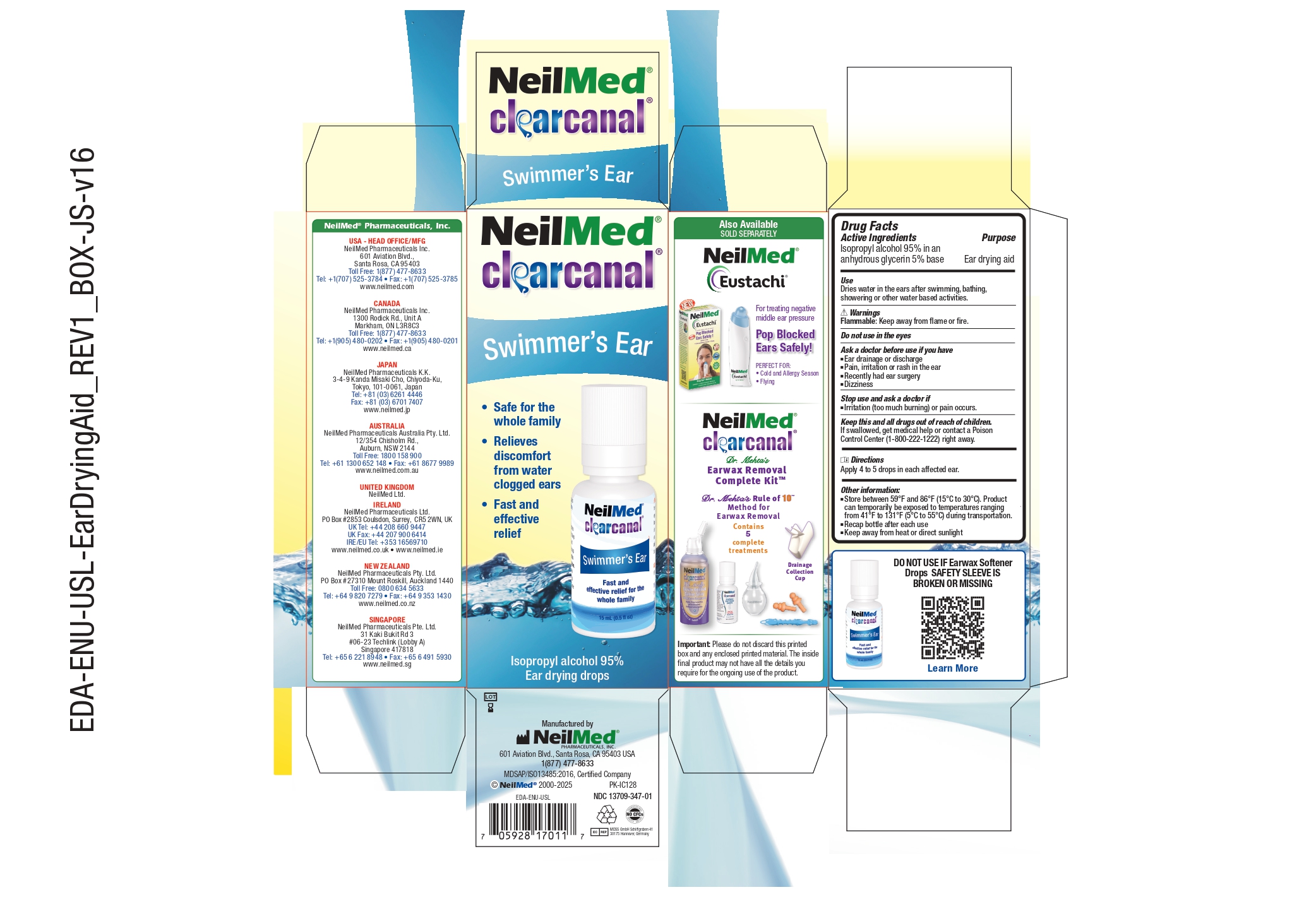 DRUG LABEL: Swimmers Ear
NDC: 13709-347 | Form: SOLUTION/ DROPS
Manufacturer: Neilmed Pharmaceuticals Inc.
Category: otc | Type: HUMAN OTC DRUG LABEL
Date: 20251113

ACTIVE INGREDIENTS: ISOPROPYL ALCOHOL 950 mg/1 mL
INACTIVE INGREDIENTS: GLYCERIN

Swimmer's Ear

Drug Facts: Active Ingredient

Isopropyl alcohol 95% in an anhydrous glycerin 5% base

Purpose

Ear drying aid

Use:

- Dries water in the ears after swimming, bathing, showering, or other water-based activities.

Warnings: Flammable:

Keep away from flame or fire

Do not use

in the eyes

Ask a doctor before use if you have

- Ear drainage or discharge.
- Pain, irritation, or rash in the ear.
- Have had ear surgery.
- Dizziness.

Stop use and ask a doctor if

- Irritation (too much burning) or pain occurs

Keep this and all drugs out of reach of children.

If swallowed, get medical help or contact a Poison Control Center (1-800-222-1222) right away.

Directions:

- Apply 4 to 5 drops in each affected ear.

Other Information:

- Store between 59°F and 86°F (15°C to 30°C). Product can temporarily be exposed to temperatures ranging from 41°F to 131°F (5°C to 55°C) during transportation.
- Recap bottle after each use
- Keep away from heat or direct sunlight

Important:

Please do not discard this printed box and any enclosed printed material. The inside final product may not have all the details you require for the ongoing use of the product.

Inactive Ingredients

Glycerin